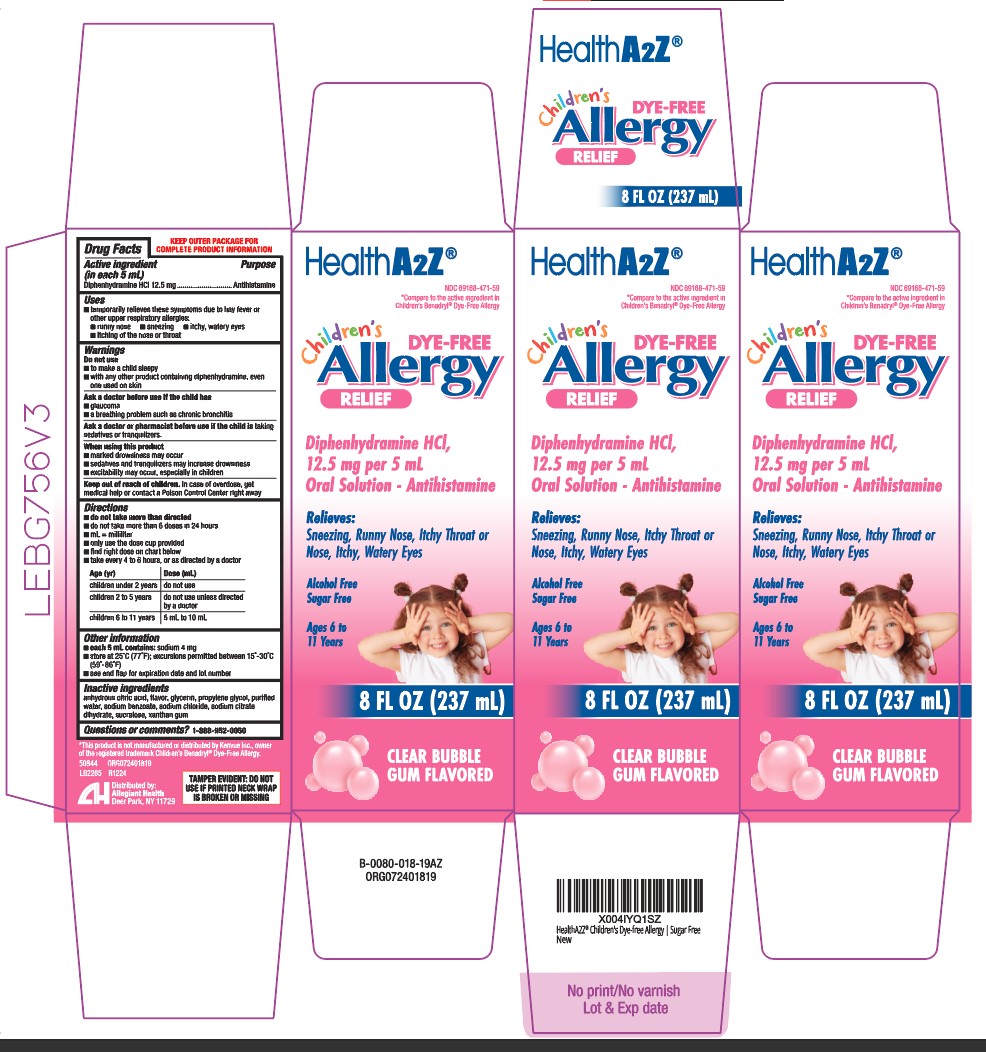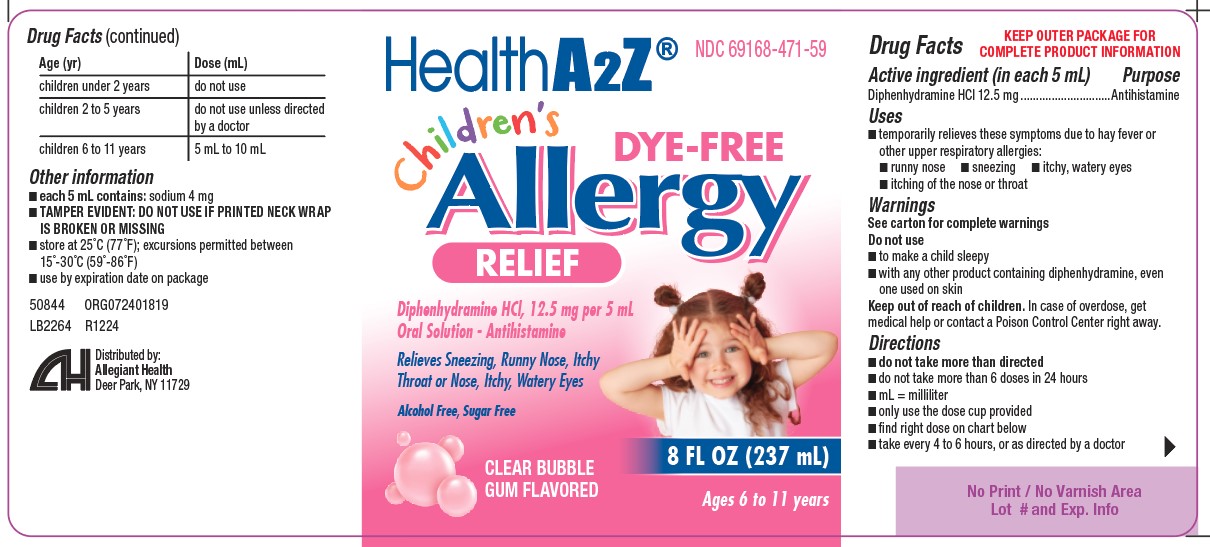 DRUG LABEL: Childrens Allergy Relief
NDC: 69168-471 | Form: LIQUID
Manufacturer: Allegiant Health
Category: otc | Type: HUMAN OTC DRUG LABEL
Date: 20250106

ACTIVE INGREDIENTS: DIPHENHYDRAMINE HYDROCHLORIDE 12.5 mg/5 mL
INACTIVE INGREDIENTS: ANHYDROUS CITRIC ACID; GLYCERIN; PROPYLENE GLYCOL; WATER; SODIUM BENZOATE; SODIUM CHLORIDE; TRISODIUM CITRATE DIHYDRATE; SUCRALOSE; XANTHAN GUM

471 - Childrens Allergy Relief

Active ingredient(s)

Diphenhydramine HCl 12.5 mg in each 5ml

Purpose

Antihistamine

Use(s)

- temporarily relieves these symptoms due to hay fever or other upper respiratory allergies:
  - runny nose
  - sneezing
  - itchy, watery eyes
  - itching of the nose or throat

Warnings

Do not use

- to make a child sleepy
- with any other product containing diphenhydramine, even one used on skin

Ask a doctor before use if

- a breathing problem such as chronic bronchitis
- glaucoma
- a sodium-restricted diet

Ask a doctor or pharmacist before use if

the child is taking sedatives or tranquilizers

When using this product

- marked drowsiness may occur
- sedatives and tranquilizers may increase drowsiness
- excitability may occur, especially in children

Keep out of reach of children

In case of overdose, get medical help or contact a Poison Control Center right away. (1-800-222-1222)

Directions

- do not take more than directed
- do not take more than 6 doses in 24 hours
- mL = milliliter
- only use the dosing cup provided
- find right dose on chart below
- take every 4 to 6 hours, or as directed by a doctor
- children under 2 years: do not use
- children 2 to 5 years: do not use unless directed by a doctor

children 6 to 11 years: 5 mL to 10 mL

Other information

each 5 ml contains: sodium 4 mg

store at 25°C (77°F); excursions permitted between 15-30°C (59°-86°F)

see end flap lot expiration date and lot number

Inactive ingredients

anhydrous citric acid, flavor, glycerin, propylene glycol, purified water, sodium
benzoate, sodium chloride, sodium citrate dihydrate, sucralose, xanthan gum

Questions/Comments

Call 1-888-952-0050 Monday Through Friday 9AM – 5PM EST.

Principal Display Panel

Allergy Relief
Children's Allergy Label